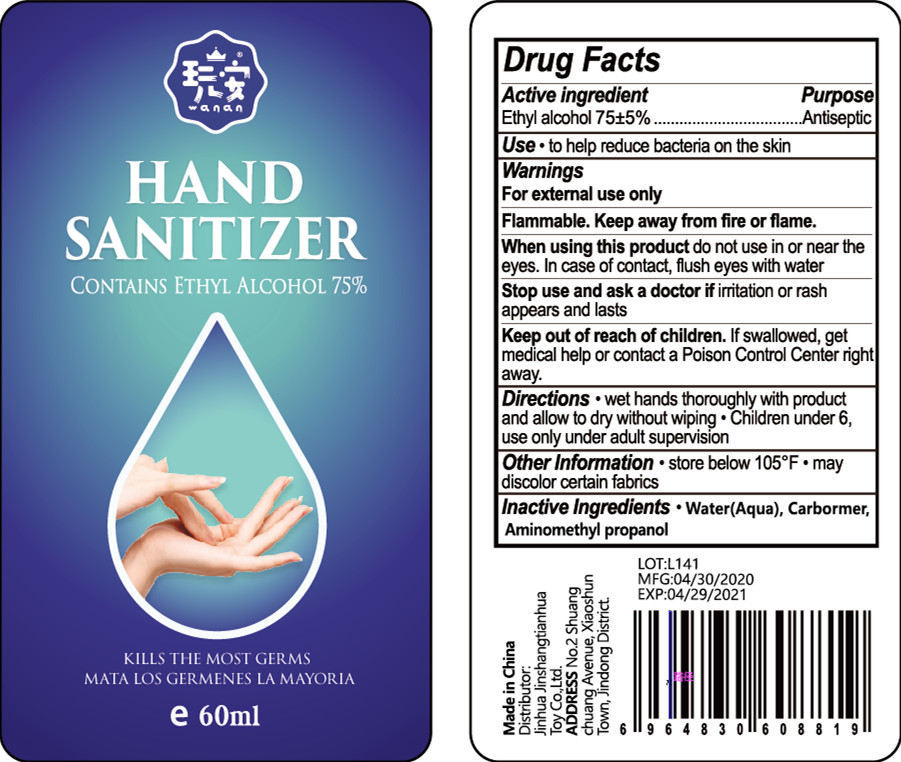 DRUG LABEL: HAND SANITIZER
NDC: 41315-001 | Form: LIQUID
Manufacturer: Jinhua Jinshangtianhua Toy Co., Ltd.
Category: otc | Type: HUMAN OTC DRUG LABEL
Date: 20200505

ACTIVE INGREDIENTS: ALCOHOL 45 mL/60 mL
INACTIVE INGREDIENTS: WATER; CARBOMER HOMOPOLYMER, UNSPECIFIED TYPE; AMINOMETHYLPROPANOL

DOSAGE AND ADMINISTRATION

store below 105°F

INACTIVE INGREDIENT

AQUA

CARBOMER

AMINOMETHYL PROPANOL

INDICATIONS AND USAGE

wet hands thoroughly with product and allow to dry without wiping

ACTIVE INGREDIENT

ALCOHOL

keep out of reach of children

PURPOSE

Disinfection
Sterilization

WARNINGS

For extermal use only Flammable. Keep away from fire or flame.When using this product do not use in or near the eyes. In case of contact, flush eyes with water Stop use and ask a doctor if iritation or rash appears and lasts Keep out of reach of children. If swallowed, get medical help or contact a Poison Control Center right away.